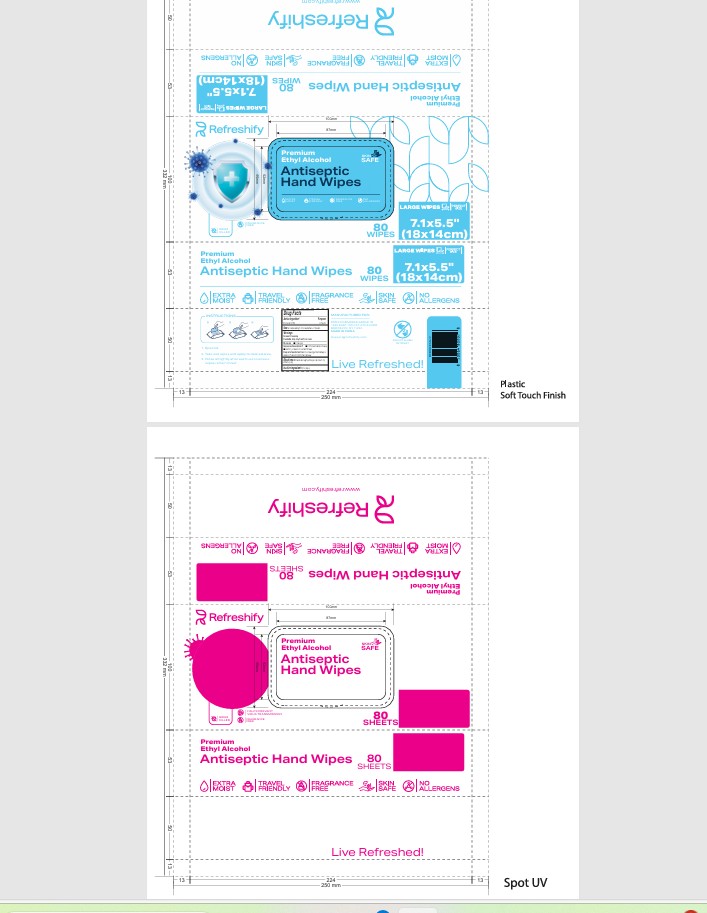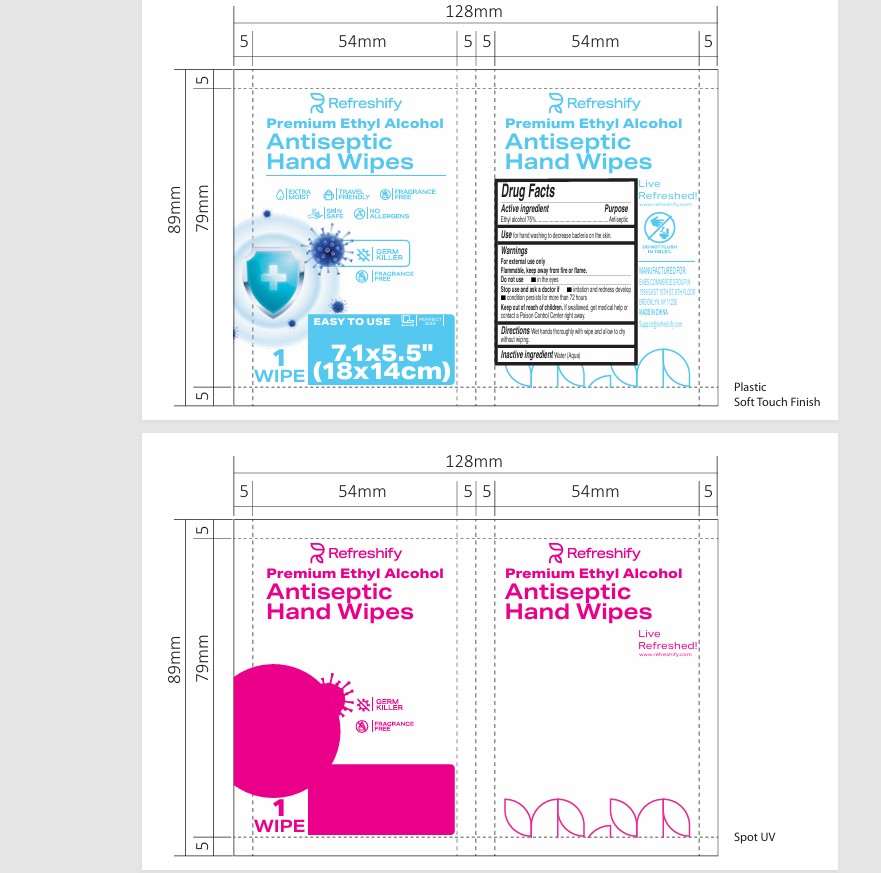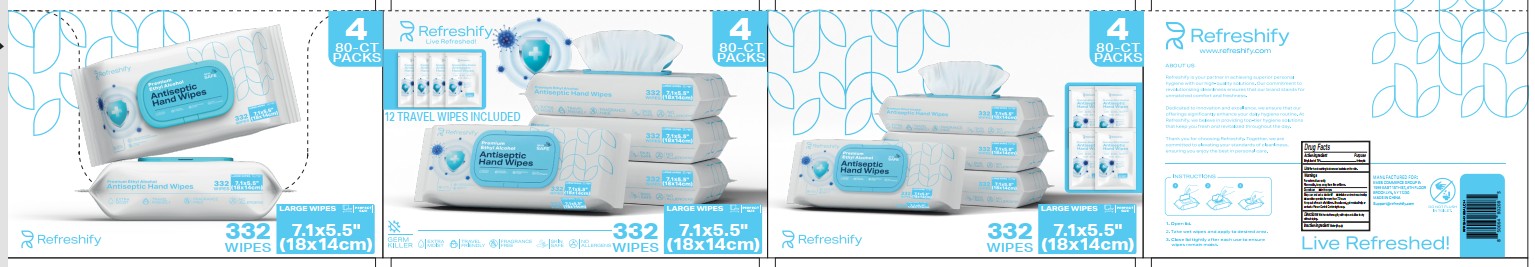 DRUG LABEL: Refreshify Antiseptic Hand Wipes
NDC: 87031-000 | Form: KIT | Route: TOPICAL
Manufacturer: Emes Commerce Group Inc.
Category: otc | Type: HUMAN OTC DRUG LABEL
Date: 20250819

ACTIVE INGREDIENTS: ALCOHOL 75 mL/100 mL; ALCOHOL 75 mL/100 mL
INACTIVE INGREDIENTS: WATER; WATER

Refreshify Antiseptic Hand Wipes

Active ingredient

Ethyl alcohol 75%

Purpose

Antiseptic

Use

for hand washing to decrease bacteria on the skin.

Warnings

For external use only
Flammable, keep away from fire or flame.

Do not use

- in the eyes

Stop use and ask a doctor if

- irritation and redness develop
- condition persists for more than 72 hours

Keep out of reach of children.

If swallowed, get medical help or contact a Poison Control Center right away.

Directions

Wet hands thoroughly with wipe and allow to dry without wiping.

Inactive ingredient

Water (Aqua)